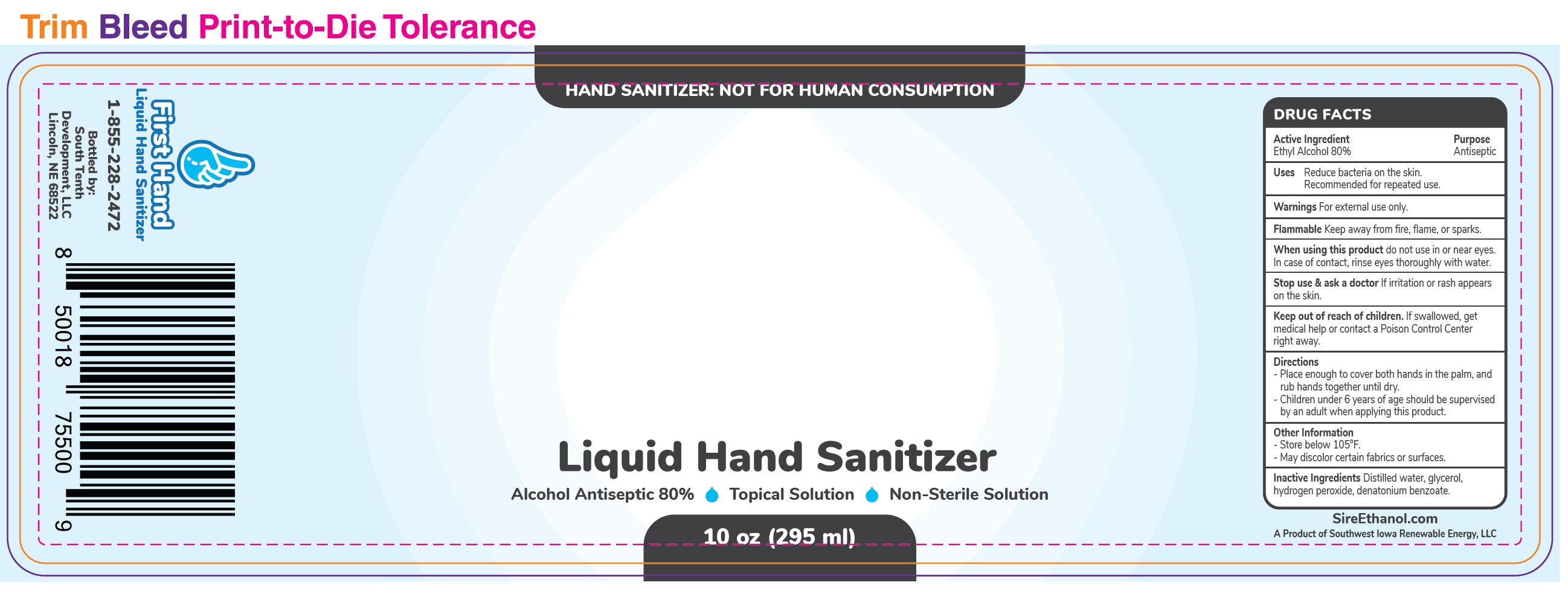 DRUG LABEL: First Hand Hand Sanitizer
NDC: 78705-000 | Form: LIQUID
Manufacturer: South Tenth Development, LLC
Category: otc | Type: HUMAN OTC DRUG LABEL
Date: 20200615

ACTIVE INGREDIENTS: ALCOHOL 0.8 mL/1 mL
INACTIVE INGREDIENTS: WATER; GLYCERIN; HYDROGEN PEROXIDE; DENATONIUM BENZOATE

"First Hand" Hand Sanitizer

Active Ingredient

Ethyl Alcohol 80%

Purpose

Antiseptic

Uses

Reduce bacteria on the skin. Recommended for repeated use

Warnings

For external use only.

Flammable Keep away from fire, flame, or sparks

When using this product

do not use in or near eyes. In case of contact, rinse eyes thoroughly with water

Stop use & ask a doctor

If irritation or rash appears on the skin.

Keep out of reach of children.

If swallowed, get medical help or contact a Poison Control Center right away.

Directions

- Place enough to cover both hands in the palm, and rub hands together until dry.
- Children under 6 years of age should be supervised by an adult when applying this product.

Other Information

- Store below 105°F.
- May discolor certain fabrics or surfaces.

Inactive Ingredients

Distilled water, glycerol, hydrogen peroxide, denatonium benzoate.